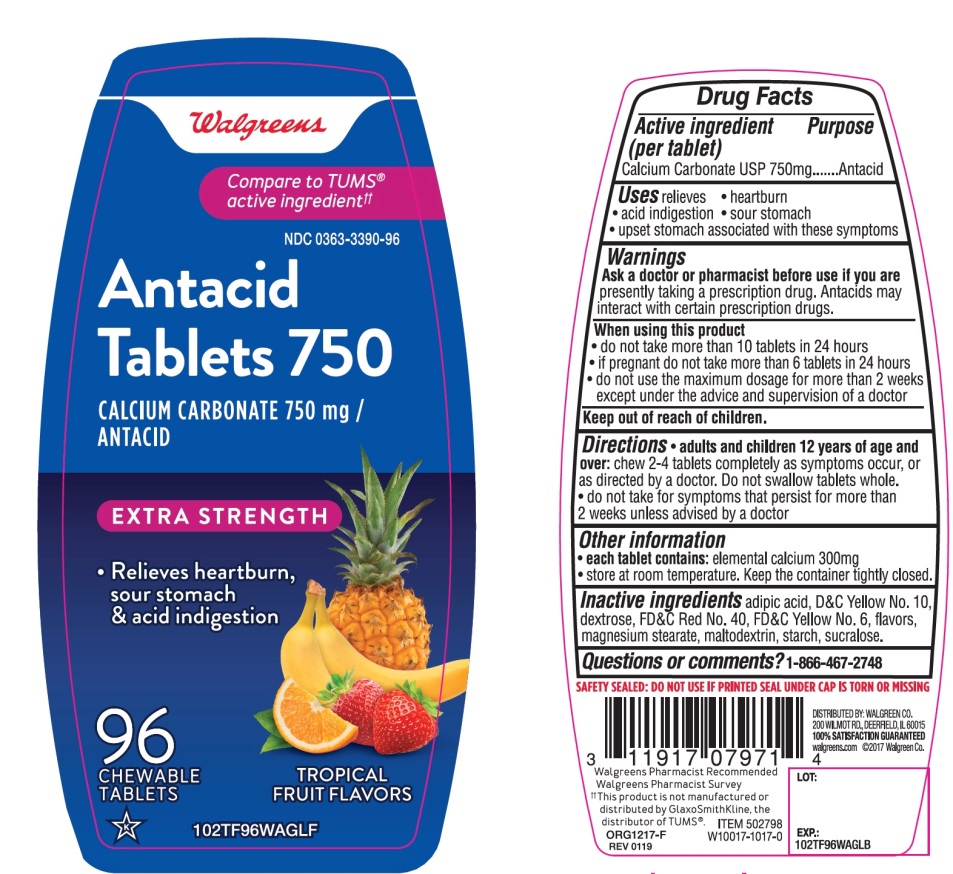 DRUG LABEL: Antacid Extra Strength
NDC: 0363-3390 | Form: TABLET, CHEWABLE
Manufacturer: WALGREEN CO.
Category: otc | Type: HUMAN OTC DRUG LABEL
Date: 20251125

ACTIVE INGREDIENTS: CALCIUM CARBONATE 750 mg/1 1
INACTIVE INGREDIENTS: ADIPIC ACID; D&C YELLOW NO. 10; DEXTROSE, UNSPECIFIED FORM; FD&C RED NO. 40; FD&C YELLOW NO. 6; MAGNESIUM STEARATE; MALTODEXTRIN; STARCH, CORN; SUCRALOSE

Walgreens Extra Strength Tropical Fruit Flavors 96 Chewable Tablets

Active ingredient (per tablet)

Calcium Carbonate USP 750mg

Purpose

Antacid

Uses

relieves:

- heartburn
- sour stomach
- acid indigestion
- upset stomach associated with these symptoms

Warnings

Ask a doctor or pharmacist before use if you arepresently taking a prescription drug. Antacids may interact with certain prescription drugs.

When using this product

- do not take more than 10 tablets in 24 hours
- if pregnant do not take more than 6 tablets in 24 hours
- do not use the maximum dosage for more than 2 weeks except under the advice and supervision of a doctor

Directions

- adults and children 12 years of age and older:chew 2-4 tablets completely as symptoms occur, or as directed by a doctor. Do not swallow tablets whole.
- do not take for symptoms that persist for more than 2 weeks unless advised by a doctor

Other information

- each tablet contains:elemental calcium 300mg
- store at room temperature. Keep the container tightly closed

SAFETY SEALED: DO NOT USE IF PRINTED SEAL UNDER CAP IS TORN OR MISSING.

Inactive ingredients

adipic acid, D&C Yellow No. 10, dextrose, FD&C Red No. 40, FD &C Yellow No. 6, flavors, magnesium stearate, maltodextrin, starch, sucralose.

Questions or comments?

1-866-467-2748

Package/Label Principal Display Panel

Walgreens

Compare to TUMS®active ingredients††

NDC 0363-3390-96

Antacid Tablets 750

CALCIUM CARBONATE 750 mg/ ANTACID

EXTRA STRENGTH

- Relieves heartburn, sour stomach & acid indigestion

TROPICAL FRUIT FLAVORS

96 CHEWABLE TABLETS

GLUTEN-FREE

Walgreens Pharmacist Recommended

Walgreens Pharmacist Survey

DISTRIBUTED BY: WALGREEN CO.

200 WILMOT RD., DEERFIELD, IL 60015

100 % SATISFACTION GUARANTEED

walgreens.com ©2017 Walgreen Co.

††This product is not manufactured or distributed by GlaxoSmithKline, the distributor of TUMS®.

ORG1217-F

REV0119